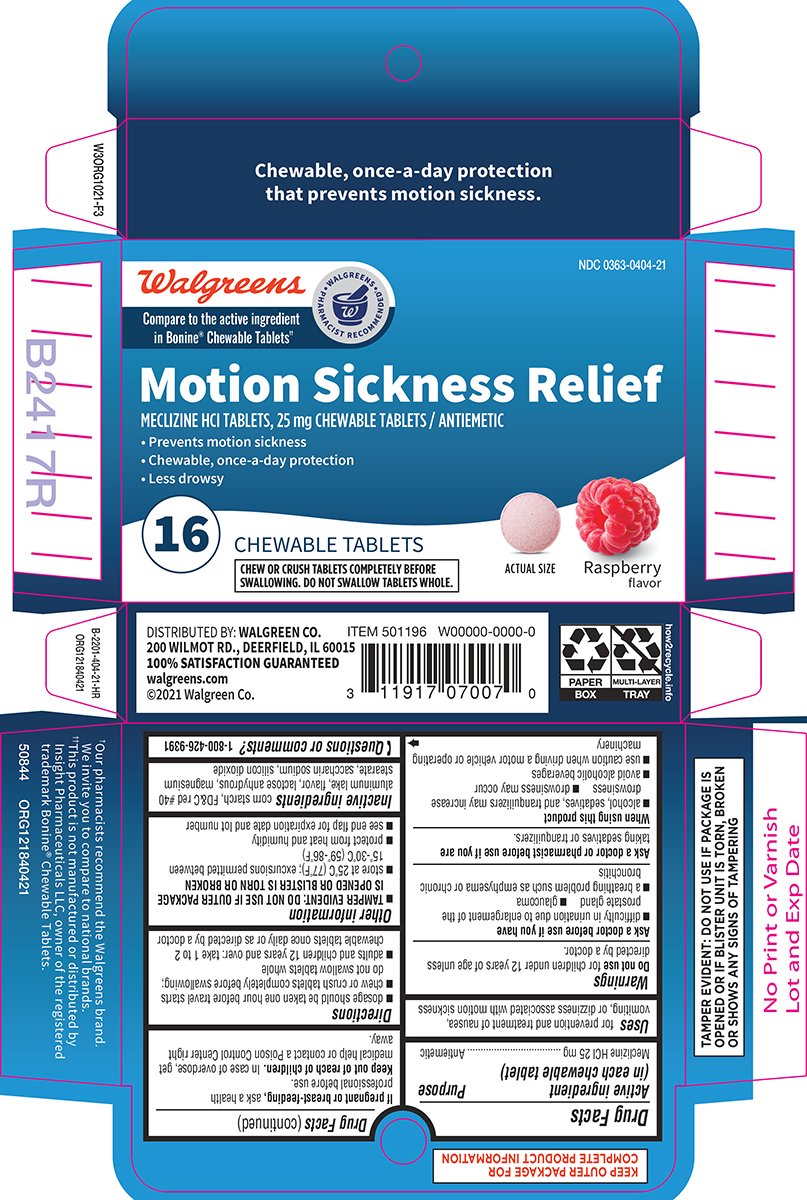 DRUG LABEL: Motion Sickness Relief
NDC: 0363-0404 | Form: TABLET, CHEWABLE
Manufacturer: Walgreen Company
Category: otc | Type: HUMAN OTC DRUG LABEL
Date: 20250618

ACTIVE INGREDIENTS: MECLIZINE HYDROCHLORIDE 25 mg/1 1
INACTIVE INGREDIENTS: STARCH, CORN; FD&C RED NO. 40; ANHYDROUS LACTOSE; MAGNESIUM STEARATE; SACCHARIN SODIUM; SILICON DIOXIDE

Walgreens 44-404 Delisted

Active ingredient (in each chewable tablet)

Meclizine HCl 25 mg

Purpose

Antiemetic

Uses

for prevention and treatment of nausea, vomiting, or dizziness associated with motion sickness

Warnings

Do not use

for children under 12 years of age unless directed by a doctor.

Ask a doctor before use if you have

- difficulty in urination due to enlargement of the prostate gland
- glaucoma
- a breathing problem such as emphysema or chronic bronchitis

Ask a doctor or pharmacist before use if you are

taking sedatives or tranquilizers.

When using this product

- alcohol, sedatives, and tranquilizers may increase drowsiness
- drowsiness may occur
- avoid alcoholic beverages
- use caution when driving a motor vehicle or operating machinery

If pregnant or breast-feeding,

ask a health professional before use.

Keep out of reach of children.

In case of overdose, get medical help or contact a Poison Control Center right away.

Directions

- dosage should be taken one hour before travel starts
- chew or crush tablets completely before swallowing; do not swallow tablets whole
- adults and children 12 years and over: take 1 to 2 chewable tablets once daily or as directed by a doctor

Other information

- TAMPER EVIDENT: DO NOT USE IF OUTER PACKAGE IS OPENED OR BLISTER IS TORN OR BROKEN
- store at 25°C (77°F); excursions permitted between 15°-30°C (59°-86°F)
- protect from heat and humidity
- see end flap for expiration date and lot number

Inactive ingredients

corn starch, FD&C red #40 aluminum lake, flavor, lactose anhydrous, magnesium stearate, saccharin sodium, silicon dioxide

Questions or comments?

1-800-426-9391

Principal Display Panel

Walgreens

Compare to the active ingredient
in Bonine® Chewable Tablets††

WALGREENS PHARMACIST RECOMMENDED†

NDC 0363-0404-21

Motion Sickness Relief
MECLIZINE HCl TABLETS, 25 mg CHEWABLE TABLETS / ANTIEMETIC

• Prevents motion sickness
• Chewable, once-a-day protection
• Less drowsy

16 CHEWABLE TABLETS

CHEW OR CRUSH TABLETS COMPLETELY BEFORE
SWALLOWING. DO NOT SWALLOW TABLETS WHOLE.

ACTUAL SIZE

Raspberry
flavor

Chewable, once-a-day protection
that prevents motion sickness.

TAMPER EVIDENT: DO NOT USE IF PACKAGE IS
OPENED OR IF BLISTER UNIT IS TORN, BROKEN
OR SHOWS ANY SIGNS OF TAMPERING

†Our pharmacists recommend the Walgreens brand.
We invite you to compare to national brands.
††This product is not manufactured or distributed by
Insight Pharmaceuticals LLC, owner of the registered
trademark Bonine® Chewable Tablets.
50844 ORG121840421

DISTRIBUTED BY: WALGREEN CO.
200 WILMOT RD., DEERFIELD, IL 60015
100% SATISFACTION GUARANTEED
walgreens.com
©2021 Walgreen Co.

Walgreens 44-404